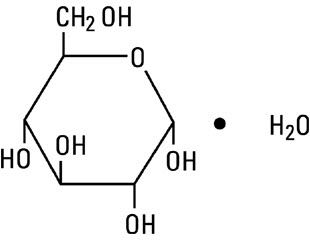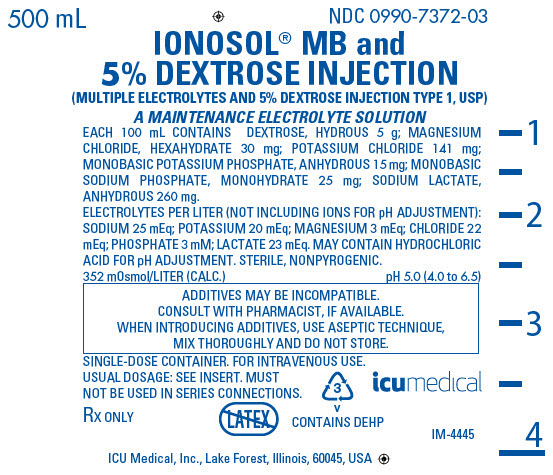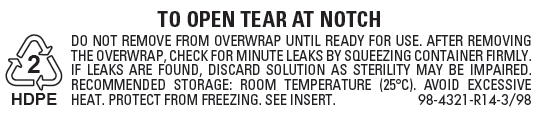 DRUG LABEL: Ionosol MB and Dextrose
NDC: 0990-7372 | Form: INJECTION, SOLUTION
Manufacturer: ICU Medical Inc.
Category: prescription | Type: HUMAN PRESCRIPTION DRUG LABEL
Date: 20251030

ACTIVE INGREDIENTS: DEXTROSE MONOHYDRATE 5 g/100 mL; SODIUM LACTATE 260 mg/100 mL; POTASSIUM CHLORIDE 141 mg/100 mL; MAGNESIUM CHLORIDE 30 mg/100 mL; MONOBASIC POTASSIUM PHOSPHATE 15 mg/100 mL; SODIUM PHOSPHATE, MONOBASIC, MONOHYDRATE 25 mg/100 mL
INACTIVE INGREDIENTS: WATER; HYDROCHLORIC ACID

Ionosol® MB and 5% Dextrose Injection

(MULTIPLE ELECTROLYTES AND 5% DEXTROSE INJECTION TYPE 1, USP)

A MAINTENANCE ELECTROLYTE SOLUTION

Flexible Plastic Container

Rx only

DESCRIPTION

Ionosol MB and 5% Dextrose Injection (Multiple Electrolytes and 5% Dextrose Injection Type 1, USP) is a sterile, nonpyrogenic solution designed for intravenous administration. The solution is formulated to provide fluid and electrolytes for treatment of dehydration and acidosis.

Each 100 mL contains dextrose, hydrous 5 g; sodium lactate, anhydrous 260 mg; potassium chloride 141 mg; magnesium chloride, hexahydrate 30 mg; monobasic potassium phosphate, anhydrous 15 mg; and monobasic sodium phosphate, monohydrate 25 mg.

Each liter contains 25 mEq sodium (Na^+); 20 mEq potassium (K^+); 3 mEq magnesium (Mg^++); 22 mEq chloride (Cl¯); 3 mM of phosphate (PO4≡); and 23 mEq lactate (CH3CH(OH)COO¯).

The electrolyte content is hypotonic (100 mOsmol/L) in relation to the extracellular fluid (1pprox.. 280 mOsmol/L). The osmolarity for the total solution is 352 mOsmol/L (calc.). May contain hydrochloric acid for pH adjustment. pH is 5.0 (4.0 to 6.5).

Dextrose, USP, hydrous is chemically designated C6H12O6 • H2O (D-glucose, monohydrate), a hexose sugar freely soluble in water. Dextrose, hydrous has the following structural formula:

Magnesium Chloride, USP, hexahydrate is chemically designated MgCl2 • 6H2O, colorless flakes or crystals very soluble in water.

Potassium Chloride, USP is chemically designated KCl, a white granular powder freely soluble in water.

Monobasic Potassium Phosphate, NF, anhydrous is chemically designated KH2PO4, colorless crystals or white granular powder freely soluble in water.

Sodium Lactate, USP is chemically designated CH3CH(OH)COONa, a 60% aqueous solution miscible in water.

Monobasic Sodium Phosphate, USP, monohydrate is chemically designated NaH2PO4• H2O, white crystals or granules freely soluble in water.

Water for Injection, USP is chemically designated H2O.

The flexible plastic container is fabricated from a specially formulated polyvinylchloride. Water can permeate from inside the container into the overwrap but not in amounts sufficient to affect the solution significantly. Solutions inside the plastic container also can leach out certain of their chemical components in very small amounts before the expiration period is attained. However, the safety of the plastic has been confirmed by tests in animals according to USP biological standards for plastic containers.

CLINICAL PHARMACOLOGY

Ionosol MB and 5% Dextrose Injection contains a hypotonic concentration of electrolytes with dextrose. The letters "MB" mean "modified Butler's" solution; the modified solution contains 5 mEq less sodium, 5 mEq more potassium, and 3 mEq added magnesium, as compared with the original Butler's solution. The modified solution can be used in pediatric patients for treatment of dehydration, acidosis, diarrhea, or burns, and in adults for postoperative fluid and electrolyte therapy.

Solutions containing dextrose restore blood glucose levels and provide calories. Carbohydrate in the form of dextrose may aid in minimizing liver glycogen depletion and exerts a protein-sparing action. Dextrose injected parenterally undergoes oxidation to carbon dioxide and water.

The lactate anion provides an alkalizing effect resulting from simultaneous removal by the liver of lactate and hydrogen ions. In the liver, the lactate is metabolized to glycogen which is ultimately converted to carbon dioxide and water by oxidative metabolism.

The lactate anion acts as a source (alternate) of bicarbonate when normal production and utilization of lactic acid is not impaired as a result of disordered lactate metabolism. Since metabolic conversion is dependent on the integrity of cellular oxidative processes, lactate may be inadequate or ineffective as a source of bicarbonate in patients suffering from acidosis associated with shock or other disorders involving reduced perfusion of body tissues. When oxidative activity is intact, one to two hours time is required for metabolism of lactate.

Magnesium chloride in water dissociates to provide magnesium (Mg^++) and chloride (Cl‾) ions. Magnesium is the second most plentiful cation of the intracellular fluids. It is an important cofactor for enzymatic reactions and plays an important role in neurochemical transmission and muscular excitability. Normal plasma concentration ranges from 1.5 to 2.5 or 3.0 mEq/liter. Magnesium is excreted solely by the kidney at a rate proportional to the plasma concentration and glomerular filtration.

Phosphate is one of the three major intracellular electrolytes (along with potassium and magnesium) and the largest anion component found within the cells. Its concentration and excretion are largely dependent on intake, acid-base balance and endocrine function. Its metabolism follows that of calcium in many respects. Phosphate anion in electrolyte solutions may help to repair phosphate deficiency.

Potassium chloride in water dissociates to provide potassium (K^+) and chloride (Cl‾) ions. Potassium is the chief cation of body cells (160 mEq/liter of intracellular water). It is found in low concentration in plasma and extracellular fluids (3.5 to 5.0 mEq/liter in a healthy adult and child over 10 days old; 3.5 to 6.0 mEq/liter in a child less than 10 days old). Potassium plays an important role in electrolyte balance. Normally about 80 to 90% of the potassium intake is excreted in the urine; the remainder in the stools and to a small extent, in the perspiration. The kidney does not conserve potassium well so that during fasting or in patients on a potassium-free diet, potassium loss from the body continues resulting in potassium depletion.

Water is an essential constituent of all body tissues and accounts for approximately 70% of total body weight. Average normal adult daily requirement ranges from two to three liters (1.0 to 1.5 liters each for insensible water loss by perspiration and urine production). Average normal pediatric daily requirements are based on the child's weight as described in the table below:

Weight | Fluid Requirements
Up to 10 kg | 100 mL/kg
11 to 20 kg | 1,000 mL + 50 mL/kg for
 | each kg above 10 kg
Above 20 kg | 1,500 mL + 20 mL/kg for
 | each kg above 20 kg

Water balance is maintained by various regulatory mechanisms. Water distribution depends primarily on the concentration of electrolytes in the body compartments, and sodium (Na^+) plays a major role in maintaining physiologic equilibrium.

Ionosol MB and 5% Dextrose Injection contains a hypotonic electrolyte concentration. This should not be confused with the total tonicity (electrolytes plus nonelectrolytes) of solutions containing both electrolytes and dextrose. In general, solutions providing isotonic electrolyte concentrations are most applicable to replacement of acute deficits, whereas hypotonic electrolyte concentrations are best suited for parenteral maintenance of water requirements when only small quantities of electrolytes are desired.

INDICATIONS AND USAGE

Ionosol MB and 5% Dextrose Injection is indicated for intravenous administration to infants for treatment of dehydration, acidosis, diarrhea, and burns, but only after administration of an initial priming solution: 15 mL of 5% dextrose and 0.45% Sodium Chloride Injection/kg of body weight.

In adults, Ionosol MB and 5% Dextrose Injection is indicated postoperatively for intravenous fluid and electrolyte maintenance therapy, with a small amount of carbohydrate calories for reducing catabolism of endogenous protein reserves.

CONTRAINDICATIONS

Solutions containing potassium are contraindicated in diseases where high potassium levels may be encountered.

WARNINGS

Solutions which contain potassium ions should be used with great care, if at all, in patients with hyperkalemia, severe renal failure and in conditions in which potassium retention is present.

Solutions containing sodium ions should be used with great care, if at all, in patients with congestive heart failure, severe renal insufficiency and in clinical states in which there exists edema with sodium retention.

In patients with diminished renal function, administration of solutions containing sodium or potassium ions may result in sodium or potassium retention.

Solutions containing lactate ions should be used with great care, if at all, in patients with metabolic or respiratory alkalosis. The administration of lactate ions should be done with great care in those conditions in which there is an increased level or an impaired utilization of lactate ions, such as severe hepatic insufficiency.

The intravenous administration of Ionosol MB and 5% Dextrose Injection can cause fluid and/or solute overloading resulting in dilution of serum electrolyte concentrations, overhydration, congested states or pulmonary edema.

The risk of dilutional states is inversely proportional to the electrolyte concentrations of administered parenteral solutions. The risk of solute overload causing congested states with peripheral and pulmonary edema is directly proportional to the electrolyte concentrations of such solutions.

PRECAUTIONS

Clinical evaluation and periodic laboratory determinations are necessary to monitor changes in fluid balance, electrolyte concentrations and acid-base balance during prolonged parenteral therapy or whenever the condition of the patient warrants such evaluation.

Caution must be exercised in the administration of parenteral fluids, especially those containing sodium ions, to patients receiving corticosteroids or corticotropin.

Solutions containing lactate ions should be used with caution as excess administration may result in metabolic alkalosis.

Solutions containing dextrose should be used with caution in patients with known subclinical or overt diabetes mellitus.

Do not administer unless solution is clear and container is undamaged. Discard unused portion.

Pregnancy Category C.

Animal reproduction studies have not been conducted with Ionosol solutions. It is also not known whether Ionosol solutions can cause fetal harm when administered to a pregnant woman or can affect reproduction capacity. Ionosol solutions should be given to a pregnant woman only if clearly needed.

Geriatric Use:

An evaluation of current literature revealed no clinical experience identifying differences in response between elderly and younger patients. In general, dose selection for an elderly patient should be cautious, usually starting at the low end of the dosing range, reflecting the greater frequency of decreased hepatic, renal, or cardiac function, and of concomitant disease or other drug therapy.

This drug is known to be substantially excreted by the kidney, and the risk of toxic reactions may be greater in patients with impaired renal function. Because elderly patients are more likely to have decreased renal function, care should be taken in dose selection, and it may be useful to monitor renal function.

Pediatric Use:

The safety and effectiveness in the pediatric population are based on the similarity of the clinical conditions of the pediatric and adult populations. In neonates or very small infants the volume of fluid may affect fluid and electrolyte balance.

Frequent monitoring of serum glucose concentrations is required when dextrose is prescribed to pediatric patients, particularly neonates and low birth weight infants.

In very low birth weight infants, excessive or rapid administration of dextrose injection may result in increased serum osmolality and possible intracerebral hemorrhage.

ADVERSE REACTIONS

Reactions which may occur because of the solution or the technique of administration include febrile response, infection at the site of injection, venous thrombosis or phlebitis extending from the site of injection, extravasation and hypervolemia.

If an adverse reaction does occur, discontinue the infusion, evaluate the patient, institute appropriate therapeutic countermeasures and save the remainder of the fluid for examination if deemed necessary.

OVERDOSAGE

In the event of overhydration or solute overload during therapy, re-evaluate the patient and institute appropriate corrective measures. See WARNINGS and PRECAUTIONS.

DOSAGE AND ADMINISTRATION

The dose is dependent upon the age, weight and clinical condition of the patient.

In infants, Ionosol MB and 5% Dextrose Injection is given only after administration of an initial priming solution: 15 mL of half isotonic saline in 5% dextrose and 0.45% Sodium Chloride Injection/kg of body weight, administered to small infants at a maximum rate of 0.8 mL/minute. Infants typically tolerate not more than 150 to 200 mL of Ionosol MB and 5% Dextrose Injection per kg body weight/day.

As reported in the literature, the dosage and constant infusion rate of intravenous dextrose must be selected with caution in pediatric patients, particularly neonates and low birth weight infants, because of the increased risk of hyperglycemia/hypoglycemia.

In adults, intravenous infusions of Ionosol MB and 5% Dextrose Injection are given postoperatively, at a rate not greater than 4 mL/minute.

Drug Interactions

Additives may be incompatible. Consult with pharmacist, if available. When introducing additives, use aseptic technique, mix thoroughly and do not store.

Parenteral drug products should be inspected visually for particulate matter and discoloration prior to administration. See PRECAUTIONS.

INSTRUCTIONS FOR USE

To Open:

Tear outer wrap at notch and remove solution container. Some opacity of the plastic due to moisture absorption during sterilization process may be observed. This is normal and does not affect the solution quality or safety. The opacity will diminish gradually.

If supplemental medication is desired, follow directions below before preparing for administration.

To Add Medication

1. Prepare additive port.
2. Using aseptic technique and an additive delivery needle of appropriate length, puncture resealable additive port at target area, inner diaphragm and inject. Withdraw needle after injecting medication.
3. The additive port may be protected by covering with an additive cap.
4. Mix container contents thoroughly.

To Administer

1. Attach administration set per manufacturer's instructions.
2. Regulate rate of administration per institutional policy.

WARNING: Do not use flexible container in series connections.

HOW SUPPLIED

Ionosol MB and 5% Dextrose Injection (Multiple Electrolytes and 5% Dextrose Injection Type 1, USP) is supplied in flexible plastic single-dose containers as follows:

NDC | Fill Volume/Container size (mL)
0409-7372-62 [Manufactured by ICU Medical, Inc., Lake Forest, Illinois, 60045 USA] | 250/250
0990-7372-62 | 250/250
0409-7372-03 [Manufactured for ICU Medical, Inc., Lake Forest, Illinois, 60045 USA] | 500/500
0990-7372-03, | 500/500
ICU Medical is transitioning NDC codes from the "0409" to a "0990" labeler code. Both NDC codes are expected to be in the market for a period of time.

Store at 20 to 25°C (68 to 77°F). [See USP Controlled Room Temperature.] Protect from freezing.

Revised: August, 2020

ICU Medical, Inc. Lake Forest, Illinois, 60045, USA
IFU0000258

PRINCIPAL DISPLAY PANEL - 500 mL Bag Label

500 mL
NDC 0990-7372-03

IONOSOL® MB and
5% DEXTROSE INJECTION
(MULTIPLE ELECTROLYTES AND 5% DEXTROSE INJECTION TYPE 1, USP)

A MAINTENANCE ELECTROLYTE SOLUTION

EACH 100 mL CONTAINS DEXTROSE, HYDROUS 5 g; MAGNESIUM
CHLORIDE, HEXAHYDRATE 30 mg; POTASSIUM CHLORIDE 141 mg;
MONOBASIC POTASSIUM PHOSPHATE, ANHYDROUS 15 mg; MONOBASIC
SODIUM PHOSPHATE, MONOHYDRATE 25 mg; SODIUM LACTATE,
ANHYDROUS 260 mg.

ELECTROLYTES PER LITER (NOT INCLUDING IONS FOR pH ADJUSTMENT):
SODIUM 25 mEq; POTASSIUM 20 mEq; MAGNESIUM 3 mEq; CHLORIDE 22
mEq; PHOSPHATE 3 mM; LACTATE 23 mEq. MAY CONTAIN HYDROCHLORIC
ACID FOR pH ADJUSTMENT. STERILE, NONPYROGENIC.

352 mOsmol/LITER (CALC.)
pH 5.0 (4.0 to 6.5)

ADDITIVES MAY BE INCOMPATIBLE.
CONSULT WITH PHARMACIST, IF AVAILABLE.
WHEN INTRODUCING ADDITIVES, USE ASEPTIC TECHNIQUE,
MIX THOROUGHLY AND DO NOT STORE.

SINGLE-DOSE CONTAINER. FOR INTRAVENOUS USE.
USUAL DOSAGE: SEE INSERT. MUST
NOT BE USED IN SERIES CONNECTIONS.

3
V

icumedical

Rx ONLY
CONTAINS DEHP

IM-4445
ICU Medical, Inc., Lake Forest, Illinois, 60045, USA

PRINCIPAL DISPLAY PANEL - Overwrap Label

TO OPEN TEAR AT NOTCH

2
HDPE

DO NOT REMOVE FROM OVERWRAP UNTIL READY FOR USE. AFTER REMOVING
THE OVERWRAP, CHECK FOR MINUTE LEAKS BY SQUEEZING CONTAINER FIRMLY.
IF LEAKS ARE FOUND, DISCARD SOLUTION AS STERILITY MAY BE IMPAIRED.
RECOMMENDED STORAGE: ROOM TEMPERATURE (25°C). AVOID EXCESSIVE
HEAT. PROTECT FROM FREEZING. SEE INSERT.
98-4321-R14-3/98